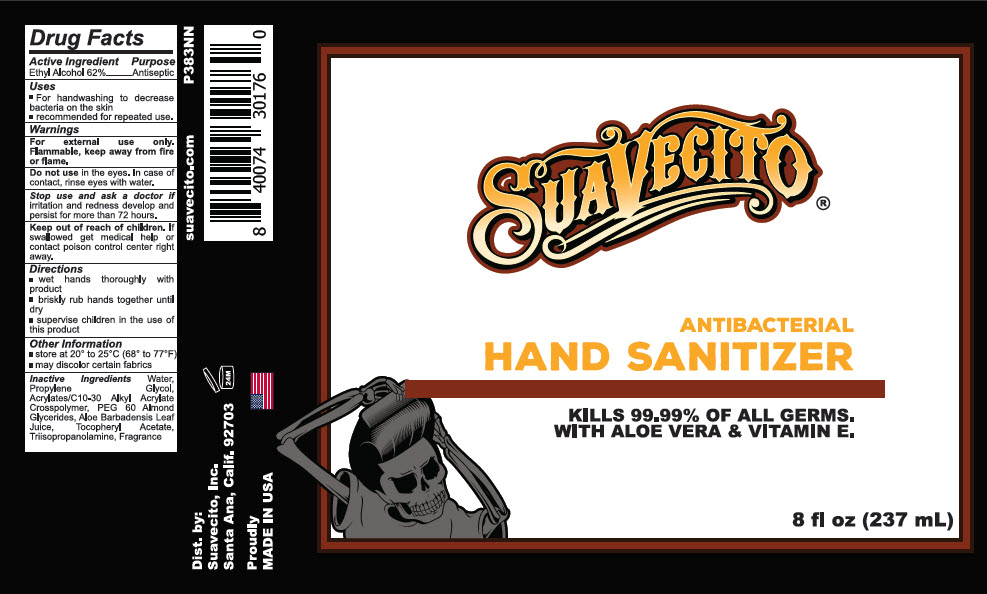 DRUG LABEL: Antibacterial Hand Sanitizer
NDC: 74866-714 | Form: GEL
Manufacturer: Suavecito,Inc.
Category: otc | Type: HUMAN OTC DRUG LABEL
Date: 20200415

ACTIVE INGREDIENTS: alcohol 62 mL/100 mL
INACTIVE INGREDIENTS: Propylene Glycol; water; PEG-60 ALMOND GLYCERIDES; aloe vera leaf; .ALPHA.-TOCOPHEROL ACETATE; triisopropanolamine; CARBOMER INTERPOLYMER TYPE B (ALLYL PENTAERYTHRITOL CROSSLINKED)

Antibacterial Hand Sanitizer

Drug Facts

Active Ingredient

Ethyl Alcohol 62%

Purpose

Antiseptic

Uses

- for hand washing to decrease bacteria on the skin
- recommended for repeated use

Warnings

For external use only.

Flammable. Keep away from fire or flame.

Do not use in the eyes. In case of contact, rinse eyes with water.

Stop use and ask a doctor if irritation and redness develop and persist for more than 72 hours.

Keep Out of reach of children. If swallowed get medical help or contact poison control center right away.

Directions

- wet hands thoroughly with product
- briskly rub hands together until dry
- Supervise children in the use of this product.

Other Information

- store at 20-25° C (68 to 77°F)
- may discolor certain fabrics

Inactive Ingredients

Water, Propylene Glycol, Acrylates/C10-3- Alkyl Acrylate Crosspolymer, Peg-60, Almond Glycerides, Aloe Barbadensis Leaf Juice, Triisopropanolamine, Fragrance

Dist. by:
Suavecito, Inc.
Santa Ana, Calif. 92703

PRINCIPAL DISPLAY PANEL - 237 mL Bottle Label

SUAVECITO®

ANTIBACTERIAL
HAND SANITIZER

KILLS 99.99% OF ALL GERMS.
WITH ALOE VERA & VITAMIN E.

8 fl oz (237 mL)